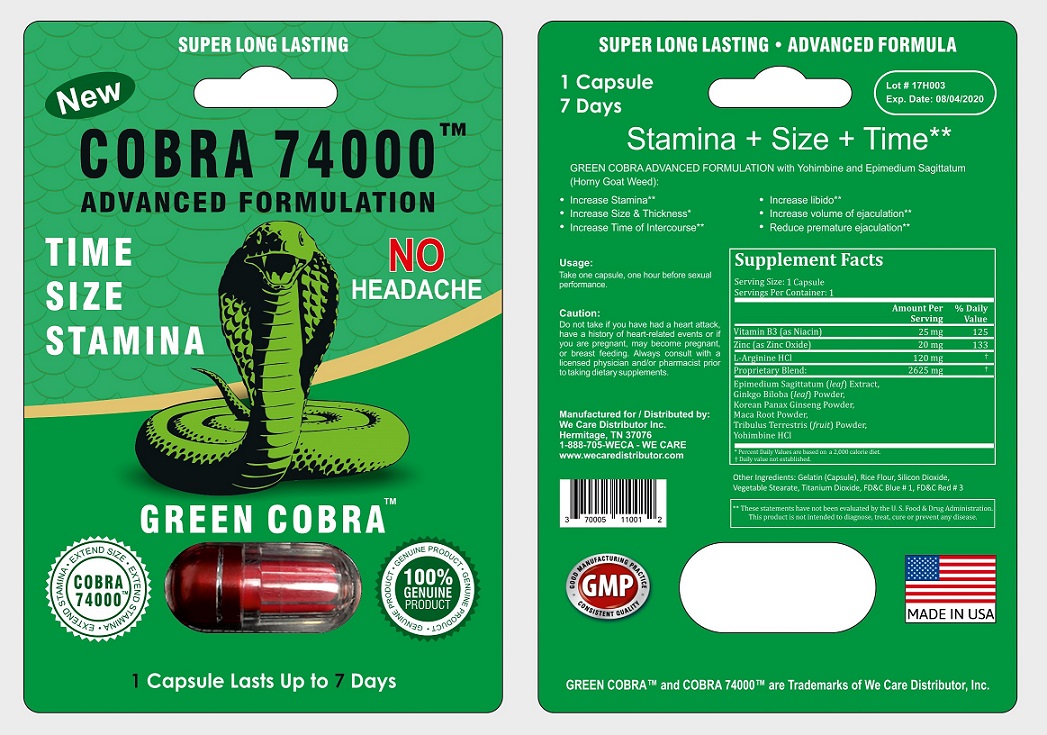 DRUG LABEL: Cobra 74000
NDC: 70005-110 | Form: CAPSULE
Manufacturer: We Care Distributor Inc.
Category: other | Type: DIETARY SUPPLEMENT
Date: 20170925

ACTIVE INGREDIENTS: NIACIN 25 mg/1 1; ZINC 20 mg/1 1; ARGININE 120 mg/1 1; EPIMEDIUM SAGITTATUM TOP 100 mg/1 1; GINKGO 1000 mg/1 1; ASIAN GINSENG 600 mg/1 1; LEPIDIUM MEYENII ROOT 400 mg/1 1; TRIBULUS TERRESTRIS FRUIT 500 mg/1 1; YOHIMBINE HYDROCHLORIDE 25 mg/1 1
INACTIVE INGREDIENTS: GELATIN, UNSPECIFIED; BROWN RICE; SILICON DIOXIDE; GLYCERYL TRISTEARATE; TITANIUM DIOXIDE; FD&C BLUE NO. 1; FD&C RED NO. 3

Cobra 74000 Advanced Formulation

STATEMENT OF IDENTITY

Men's Sexual Health Supplement

Directions

Take one capsule, one hour before sexual performance.

Warnings

Do not take if you have had a heart attack, have a history of heart-related events or if you are pregnant, may become pregnant, or breast feeding.

Precautions

Always consult with a licensed physician and/or pharmacist prior to taking dietary supplements.

Do not use if either tamper-evident seal is broken or missing.

Keep out of the reach of children.

Store in a cool, dry place.

HEALTH CLAIM

1 Capsule Lasts Up to 7 days

Stamina + Size + Time [These statements have not been evaluated by the Food and Drug Administration. This product is not intended to diagnose, treat, cure, or prevent any disease.]

- Increase Stamina
- Increase Size and Thickness
- Increase Time of Intercorse
- Increase libido
- Increase volume of ejaculation
- Reduce premature ejaculation

HEALTH CLAIM

Supplement Facts
Serving Size: 1 Capsule
Serving Per Container: 1
 | Amount Per Serving | % Daily Value [Percent Daily Values are based on a 2,000 calories diet.]
Vitamin B3 (as Niacin) | 25 mg | 125
Zinc (as Zinc Oxide) | 20 mg | 133
L-Arginine HCl | 120 mg | [Daily value not established.]
Proprietary Blend: | 2625 mg
Epimedium Sagittatum (leaf) Extract,
Ginkgo Biloba (leaf) Powder,
Korean Panax Ginseng Powder,
Maca Root Powder,
Tribulus Terrestris (fruit) Powder,
Yohimbine HCl

Other Ingredients

Gelatin (Capsule), Rice Flour, Silicon Dioxide, Vegetable Stearate, Titanium Dioxide, FD&C Blue # 1, FD&C Red # 3

HEALTH CLAIM

Manufactured for / Distributed by:
We Care Distributor Inc.
Hermitage, TN 37076

1-888-705-WECA - WE CARE
www.wecaredistributor.com